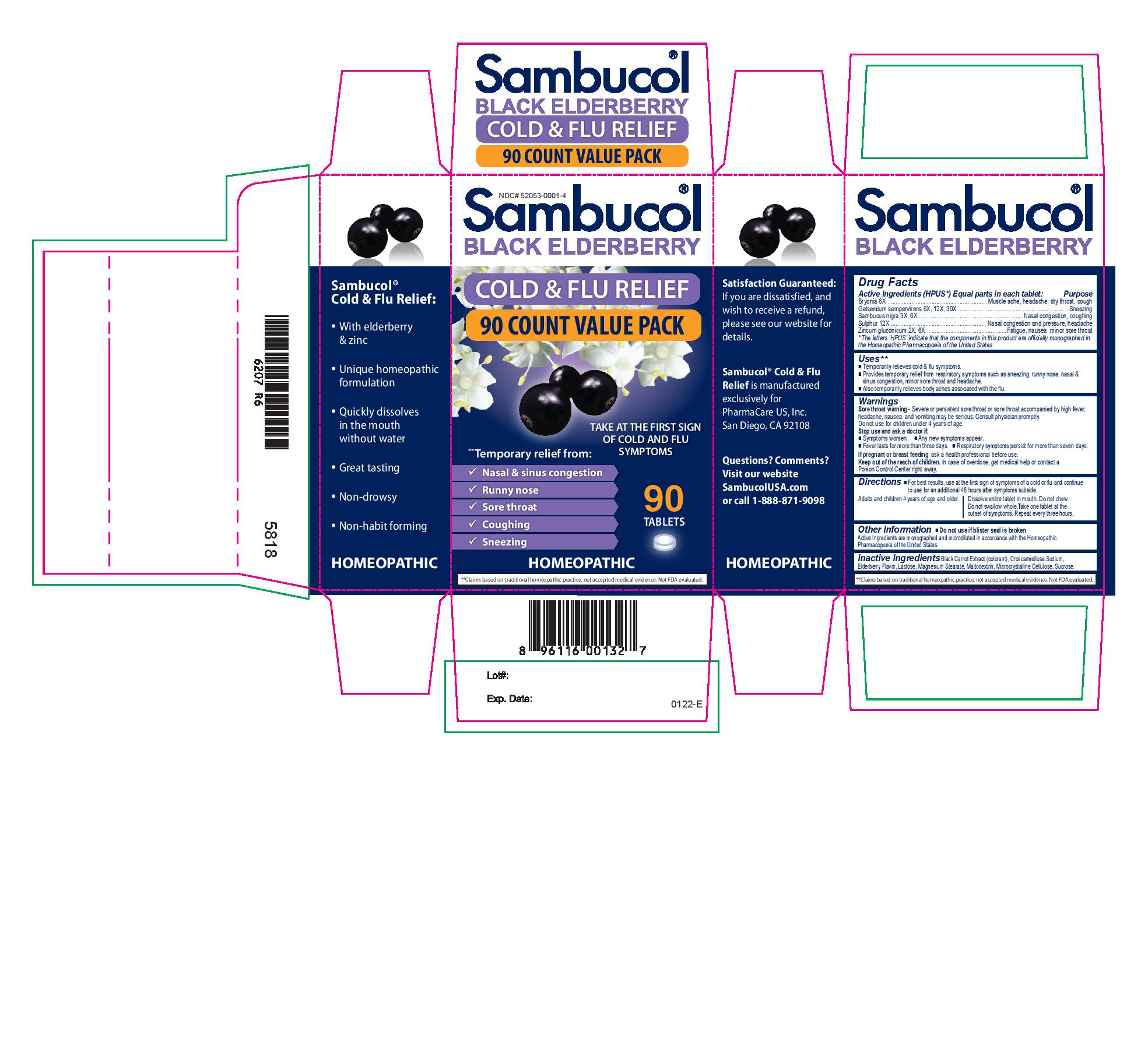 DRUG LABEL: Sambucol Cold and Flu Relief
NDC: 52053-0001 | Form: TABLET, ORALLY DISINTEGRATING
Manufacturer: PharmaCare US, Inc.
Category: homeopathic | Type: HUMAN OTC DRUG LABEL
Date: 20220412

ACTIVE INGREDIENTS: BRYONIA ALBA ROOT 6 [hp_X]/1 mg; SAMBUCUS NIGRA FLOWERING TOP 3 [hp_X]/1 mg; GELSEMIUM SEMPERVIRENS ROOT 6 [hp_X]/1 mg; ZINC GLUCONATE 2 [hp_X]/1 mg; SULFUR 12 [hp_X]/1 mg
INACTIVE INGREDIENTS: BLACK CARROT ANTHOCYANINS; MAGNESIUM STEARATE; CROSCARMELLOSE SODIUM; EUROPEAN ELDERBERRY JUICE; MALTODEXTRIN; LACTOSE, UNSPECIFIED FORM; MICROCRYSTALLINE CELLULOSE; SUCROSE

Sambucol Cold and Flu Relief

Active Ingredients

Bryonia 6X

Gelsemium sempervirens 6X, 12X, 30X

Sambucus nigra 3X, 6X

Sulphur 12X

Zincum gluconicum 2X, 6X

Purpose

Bryonia 6X................Muscle ache, headache, dry throat, cough

Gelsemium sempervirens 6X, 12X, 30X.......................Sneezing

Sambucus nigra 3X, 6X...................Nasal congestion, coughing

Sulphur 12X....................Nasal congestion and pressure, headache

Zincum gluconicum 2X, 6X..........................Fatigue, nausea, minor sore throat

* The letters 'HPUS' indicate that the components in this product are officially monographed in the Homeopathic Pharmacopoeia of the United States.

Uses

- Temporarily relieves cold & flu symptoms.
- Provides temporary relief from respiratory symptoms such as sneezing, runny nose, nasal & sinus congestion, minor sore throat and headache.
- Also temporarily relieves body aches associated with the flu.

Warnings

Sore throat warning - Severe or persistent sore throat or sore throat accompanied by high fever, headache, nausea, and vomiting may be serious. Consult physician promptly.

Do not use for children under 4 years of age.

Stop use and ask a doctor if:

- Symptoms worsen
- Any new symptoms appear
- Fever lasts for more than three days
- Respiratory symptoms persist for more than seven days

PREGNANCY OR BREAST FEEDING

If pregnant or breast feeding, ask a health professional before use.

KEEP OUT OF REACH OF CHILDREN

Keep out of the reach of children. In case of overdose, get medical help or contact a Poison Control Center right away.

Directions

For best results, use at the first sign of symptoms of a cold or flu and continue to use for an additional 48 hours after symptoms subside.

Adults and children 4 years of age and older - Dissolve entire tablet in mouth. Do not chew. Do not swallow whole. Take one tablet at the outset of symptoms. Repeat every three hours.

Other Information

- Do not use if blister seal is broken

Active ingredients are monographed and microdiluted in accordance with the Homeopathic Pharmacopoeia of the United States.

Inactive Ingredients

Black Carrot Extract (colorant), Croscarmellose Sodium, Elderberry Flavor, Lactose, Magnesium Stearate, Maltodextrin, Microcrystalline Cellulose, Sucrose.

PACKAGE LABEL

NDC# 52053-0001-4

Sambucol

Black Elderberry

Cold & Flu Relief

90 Count Family Pack

Take at the first sign of cold and flu symptoms

**Temporary relief from:

- Nasal & sinus congestion
- Runny nose
- Sore throat
- Coughing
- Sneezing

90 Tablets

Homeopathic

**Claims based on traditional homeopathic practice, not accepted medical evidence. Not FDA evaluated.